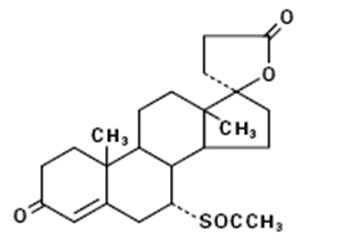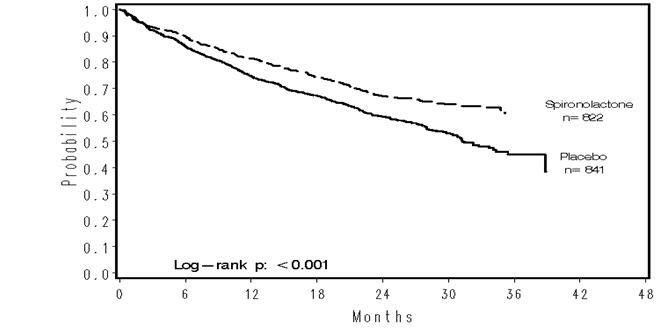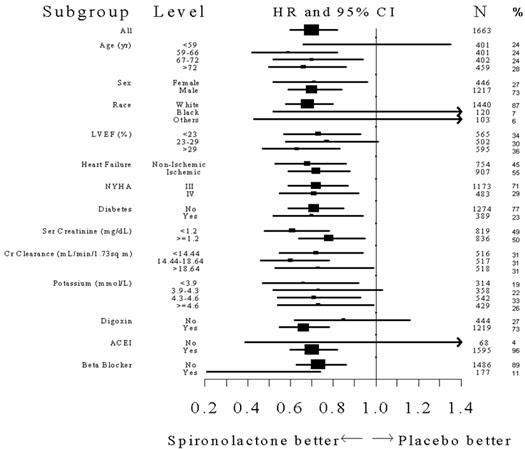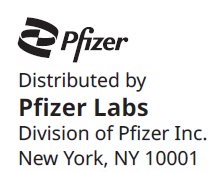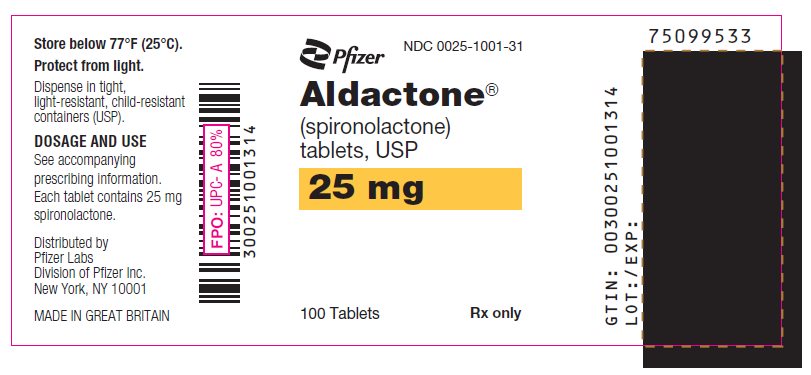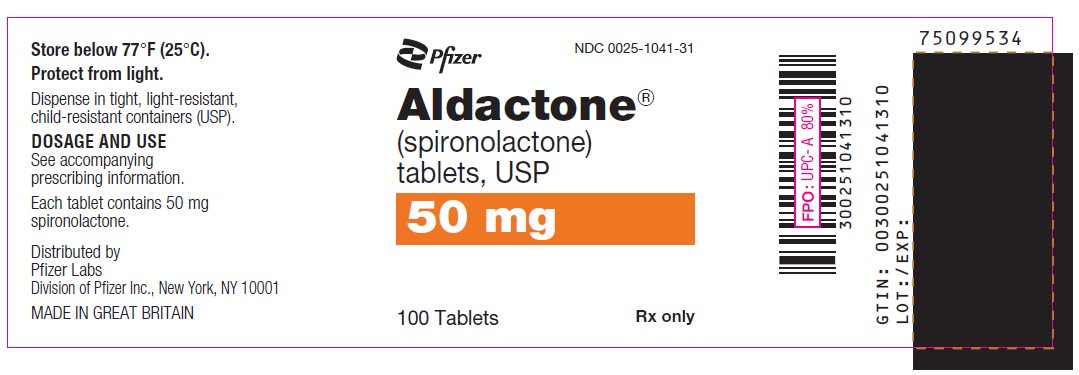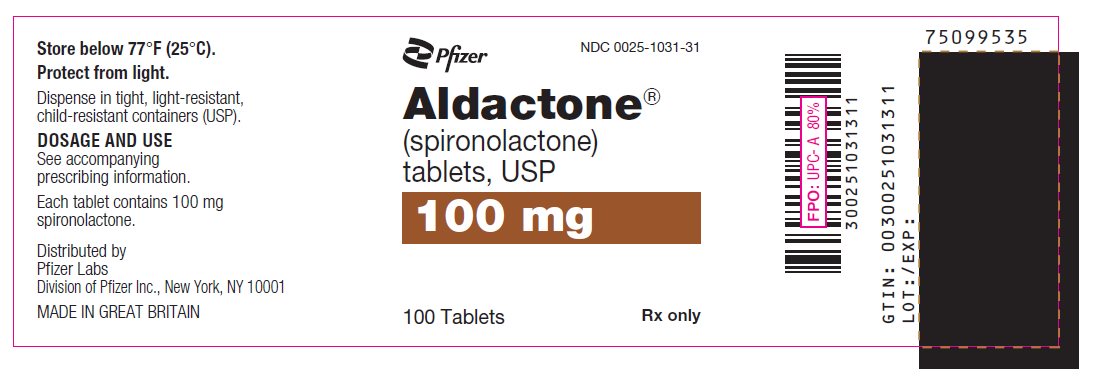 DRUG LABEL: Aldactone
NDC: 0025-1001 | Form: TABLET, FILM COATED
Manufacturer: Pfizer Laboratories Div Pfizer Inc
Category: prescription | Type: HUMAN PRESCRIPTION DRUG LABEL
Date: 20251128

ACTIVE INGREDIENTS: SPIRONOLACTONE 25 mg/1 1
INACTIVE INGREDIENTS: STARCH, CORN; FERRIC OXIDE RED; MAGNESIUM STEARATE; POVIDONE, UNSPECIFIED; TITANIUM DIOXIDE; HYPROMELLOSE 2910 (15000 MPA.S); CALCIUM SULFATE DIHYDRATE; PEPPERMINT; POLYETHYLENE GLYCOL 400; CARNAUBA WAX; STEARIC ACID

HIGHLIGHTS OF PRESCRIBING INFORMATION

These highlights do not include all the information needed to use ALDACTONE safely and effectively. See full prescribing information for ALDACTONE.
ALDACTONE® (spironolactone) tablets for oral use
Initial U.S. Approval: 1960

1 INDICATIONS AND USAGE

ALDACTONE is an aldosterone antagonist indicated for:

- The treatment of NYHA Class III–IV heart failure and reduced ejection fraction to increase survival, manage edema, and to reduce the need for hospitalization for heart failure (1.1).
- Use as an add-on therapy for the treatment of hypertension, to lower blood pressure. Lowering blood pressure reduces the risk of fatal and nonfatal cardiovascular events, primarily strokes and myocardial infarctions (1.2).
- The management of edema in adult patients who are cirrhotic when edema is not responsive to fluid and sodium restrictions and in the setting of nephrotic syndrome when treatment of the underlying disease, restriction of fluid and sodium intake, and the use of other diuretics produce an inadequate response (1.3).
- Treatment of primary hyperaldosternism for: (1.4)
  - Short-term preoperative treatment
  - Long-term maintenance for patients with discrete aldosterone-producing adrenal adenomas who are not candidates for surgery and patients with bilateral micro or macronodular adrenal hyperplasia

2 DOSAGE AND ADMINISTRATION

- Heart Failure: Initiate treatment at 25 mg once daily (2.2).
- Hypertension: Initiate treatment at 25 to 100 mg daily in either single or divided doses (2.3).
- Edema: Initiate therapy in a hospital setting and titrate slowly. The recommended initial daily dose is 100 mg in single or divided doses (2.4).
- Primary hyperaldosteronism: Initiate treatment at 100 to 400 mg in preparation for surgery. In patients unsuitable for surgery use the lowest effective dosage determined for the individual patient (2.5).

3 DOSAGE FORMS AND STRENGTHS

Tablets: 25 mg, 50 mg, and 100 mg (3)

4 CONTRAINDICATIONS

ALDACTONE is contraindicated in patients with (4):

- Hyperkalemia
- Addison's disease
- Concomitant use of eplerenone

5 WARNINGS AND PRECAUTIONS

- Hyperkalemia: Monitor serum potassium within one week of initiation and regularly thereafter (5.1).
- Hypotension and Worsening Renal Function: Monitor volume status and renal function periodically (5.2).
- Electrolyte and Metabolic Abnormalities: Monitor serum electrolytes, uric acid and blood glucose periodically (5.3).
- Gynecomastia: ALDACTONE can cause gynecomastia (5.4).

6 ADVERSE REACTIONS

The most common adverse reaction with ALDACTONE treatment is gynecomastia (5.4, 6).
To report SUSPECTED ADVERSE REACTIONS, contact Pfizer, Inc. at 1-800-438-1985 or FDA at 1-800-FDA-1088 or www.fda.gov/medwatch.

7 DRUG INTERACTIONS

- Agents increasing serum potassium: Concomitant administration can lead to hyperkalemia (5.1, 7.1).
- Lithium: Increased risk of lithium toxicity (7.2).
- NSAIDs: May reduce the diuretic, natriuretic and antihypertensive effect of ALDACTONE (7.3).
- Digoxin: ALDACTONE can interfere with radioimmunologic assays of digoxin exposure (7.4).
- Cholestyramine: Hyperkalemic metabolic acidosis has been reported with concomitant use (7.5).
- Acetylsalicylic Acid (ASA): ASA may reduce the efficacy of ALDACTONE (7.6).
- Abiraterone: May increase prostate-specific antigen (PSA) levels (7.7).
- Mitotane: Avoid concomitant use of ALDACTONE and mitotane (7.8).

8 USE IN SPECIFIC POPULATIONS

- Pregnancy: Based on animal data, ALDACTONE may affect sex differentiation of the male during embryogenesis (8.1)

FULL PRESCRIBING INFORMATION

1 INDICATIONS AND USAGE

1.1 Heart Failure

ALDACTONE is indicated for treatment of NYHA Class III–IV heart failure and reduced ejection fraction to increase survival, manage edema, and reduce the need for hospitalization for heart failure.

ALDACTONE is usually administered in conjunction with other heart failure therapies.

1.2 Hypertension

ALDACTONE is indicated as add-on therapy for the treatment of hypertension, to lower blood pressure in patients who are not adequately controlled on other agents. Lowering blood pressure reduces the risk of fatal and nonfatal cardiovascular events, primarily strokes and myocardial infarctions. These benefits have been seen in controlled trials of antihypertensive drugs from a wide variety of pharmacologic classes.

Control of high blood pressure should be part of comprehensive cardiovascular risk management, including, as appropriate, lipid control, diabetes management, antithrombotic therapy, smoking cessation, exercise, and limited sodium intake. Many patients will require more than one drug to achieve blood pressure goals. For specific advice on goals and management, see published guidelines, such as those of the National High Blood Pressure Education Program's Joint National Committee on Prevention, Detection, Evaluation, and Treatment of High Blood Pressure (JNC).

Numerous antihypertensive drugs, from a variety of pharmacologic classes and with different mechanisms of action, have been shown in randomized controlled trials to reduce cardiovascular morbidity and mortality, and it can be concluded that it is blood pressure reduction, and not some other pharmacologic property of the drugs, that is largely responsible for those benefits. The largest and most consistent cardiovascular outcome benefit has been a reduction in the risk of stroke, but reductions in myocardial infarction and cardiovascular mortality also have been seen regularly.

Elevated systolic or diastolic pressure causes increased cardiovascular risk, and the absolute risk increase per mmHg is greater at higher blood pressures, so that even modest reductions of severe hypertension can provide substantial benefit. Relative risk reduction from blood pressure reduction is similar across populations with varying absolute risk, so the absolute benefit is greater in patients who are at higher risk independent of their hypertension (for example, patients with diabetes or hyperlipidemia), and such patients would be expected to benefit from more aggressive treatment to a lower blood pressure goal.

Some antihypertensive drugs have smaller blood pressure effects (as monotherapy) in black patients, and many antihypertensive drugs have additional approved indications and effects (e.g., on angina, heart failure, or diabetic kidney disease). These considerations may guide selection of therapy.

1.3 Edema Associated with Hepatic Cirrhosis or Nephrotic Syndrome

ALDACTONE is indicated for the management of edema in the following settings:

- Cirrhosis of the liver when edema is not responsive to fluid and sodium restriction.
- Nephrotic syndrome when treatment of the underlying disease, restriction of fluid and sodium intake, and the use of other diuretics produce an inadequate response.

Because it increases serum potassium, ALDACTONE may be useful for treating edema when administration of other diuretics has caused hypokalemia.

1.4 Primary Hyperaldosteronism

ALDACTONE is indicated in the following settings:

- Short-term preoperative treatment of patients with primary hyperaldosteronism.
- Long-term maintenance therapy for patients with discrete aldosterone-producing adrenal adenomas who are not candidates for surgery.
- Long-term maintenance therapy for patients with bilateral micro or macronodular adrenal hyperplasia (idiopathic hyperaldosteronism).

2 DOSAGE AND ADMINISTRATION

2.1 General Considerations

ALDACTONE can be taken with or without food, but should be taken consistently with respect to food [see Clinical Pharmacology (12.3)].

2.2 Treatment of Heart Failure

In patients with serum potassium ≤5.0 mEq/L and eGFR >50 mL/min/1.73 m^2, initiate treatment at 25 mg once daily. Patients who tolerate 25 mg once daily may have their dosage increased to 50 mg once daily as clinically indicated. Patients who develop hyperkalemia on 25 mg once daily may have their dosage reduced to 25 mg every other day [see Warnings and Precautions (5.1)]. In patients with an eGFR between 30 and 50 mL/min/1.73 m^2, consider initiating therapy at 25 mg every other day because of the risk of hyperkalemia [see Use in Specific Populations (8.6)].

2.3 Treatment of Essential Hypertension

The recommended initial daily dose is 25 to 100 mg of ALDACTONE administered in either single or divided doses is recommended. Dosage can be titrated at two-week intervals. Doses greater than 100 mg/day generally do not provide additional reductions in blood pressure.

2.4 Treatment of Edema

In patients with cirrhosis, initiate therapy in a hospital setting and titrate slowly [see Use in Specific Populations (8.7)]. The recommended initial daily dosage is 100 mg of ALDACTONE administered in either single or divided doses, but may range from 25 to 200 mg daily. When given as the sole agent for diuresis, administer for at least five days before increasing dose to obtain desired effect.

2.5 Treatment of Primary Hyperaldosteronism

Administer ALDACTONE in doses of 100 to 400 mg daily in preparation for surgery. For patients who are considered unsuitable for surgery, ALDACTONE can be used as long-term maintenance therapy at the lowest effective dosage determined for the individual patient.

3 DOSAGE FORMS AND STRENGTHS

Tablets: 25 mg round, light yellow, film-coated, with SEARLE and 1001 debossed on one side and ALDACTONE and 25 on the other side.

Tablets: 50 mg oval, light orange, scored, film-coated, with SEARLE and 1041 debossed on the scored side and ALDACTONE and 50 on the other side.

Tablets: 100 mg round, peach-colored, scored, film-coated, with SEARLE and 1031 debossed on the scored side and ALDACTONE and 100 on the other side.

4 CONTRAINDICATIONS

ALDACTONE is contraindicated in the patients with:

- Hyperkalemia
- Addison's disease
- Concomitant use of eplerenone

5 WARNINGS AND PRECAUTIONS

5.1 Hyperkalemia

ALDACTONE can cause hyperkalemia. This risk is increased by impaired renal function or concomitant potassium supplementation, potassium-containing salt substitutes or drugs that increase potassium, such as angiotensin converting enzyme inhibitors and angiotensin receptor blockers [see Drug Interactions (7.1)].

Monitor serum potassium within 1 week of initiation or titration of ALDACTONE and regularly thereafter. More frequent monitoring may be needed when ALDACTONE is given with other drugs that cause hyperkalemia or in patients with impaired renal function.

If hyperkalemia occurs, decrease the dose or discontinue ALDACTONE and treat hyperkalemia.

5.2 Hypotension and Worsening Renal Function

Excessive diuresis may cause symptomatic dehydration, hypotension and worsening renal function, particularly in salt-depleted patients or those taking angiotensin converting enzyme inhibitors and angiotensin II receptor blockers. Worsening of renal function can also occur with concomitant use of nephrotoxic drugs (e.g., aminoglycosides, cisplatin, and NSAIDs). Monitor volume status and renal function periodically.

5.3 Electrolyte and Metabolic Abnormalities

In addition to causing hyperkalemia, ALDACTONE can cause hyponatremia, hypomagnesemia, hypocalcemia, hypochloremic alkalosis, and hyperglycemia. Asymptomatic hyperuricemia can occur and rarely gout is precipitated. Monitor serum electrolytes, uric acid and blood glucose periodically.

5.4 Gynecomastia

ALDACTONE can cause gynecomastia. In RALES, patients with heart failure treated with a mean dose of 26 mg of spironolactone once daily, about 9% of the male subjects developed gynecomastia. The risk of gynecomastia increases in a dose-dependent manner with an onset that varies widely from 1–2 months to over a year. Gynecomastia is usually reversible.

6 ADVERSE REACTIONS

The following clinically significant adverse reactions are described elsewhere in the labeling:

- Hyperkalemia [see Warnings and Precautions (5.1)]
- Hypotension and Worsening Renal Function [see Warnings and Precautions (5.2)]
- Electrolyte and Metabolic Abnormalities [see Warnings and Precautions (5.3)]
- Gynecomastia [see Warnings and Precautions (5.4]
- Impaired neurological function/ coma in patients with hepatic impairment, cirrhosis and ascites [see Use in Specific Populations (8.7)]

The following adverse reactions associated with the use of spironolactone were identified in clinical trials or postmarketing reports. Because these reactions were reported voluntarily from a population of uncertain size, it is not always possible to estimate their frequency, reliably, or to establish a causal relationship to drug exposure.

Digestive: Gastric bleeding, ulceration, gastritis, diarrhea and cramping, nausea, vomiting.

Reproductive: Decreased libido, inability to achieve or maintain erection, irregular menses or amenorrhea, postmenopausal bleeding, breast and nipple pain.

Hematologic: Leukopenia (including agranulocytosis), thrombocytopenia.

Hypersensitivity: Fever, urticaria, maculopapular or erythematous cutaneous eruptions, anaphylactic reactions, vasculitis.

Metabolism: Hyperkalemia, electrolyte disturbances [see Warnings and Precautions (5.1, 5.3)], hyponatremia, hypovolemia.

Musculoskeletal: Leg cramps.

Nervous system/psychiatric: Lethargy, mental confusion, ataxia, dizziness, headache, drowsiness.

Liver/biliary: A very few cases of mixed cholestatic/hepatocellular toxicity, with one reported fatality, have been reported with spironolactone administration.

Renal: Renal dysfunction (including renal failure).

Skin: Stevens-Johnson Syndrome (SJS), toxic epidermal necrolysis (TEN), drug rash with eosinophilia and systemic symptoms (DRESS), alopecia, pruritis.

7 DRUG INTERACTIONS

7.1 Drugs and Supplements Increasing Serum Potassium

Concomitant administration of ALDACTONE with potassium supplementation or drugs that can increase potassium may lead to severe hyperkalemia. In general, discontinue potassium supplementation in heart failure patients who start ALDACTONE [see Warnings and Precautions (5.1) and Clinical Pharmacology (12.3)]. Check serum potassium levels when ACE inhibitor or ARB therapy is altered in patients receiving ALDACTONE.

Examples of drugs that can increase potassium include:

- ACE inhibitors
- angiotensin receptor blockers
- non-steroidal anti-inflammatory drugs (NSAIDs)
- heparin and low molecular weight heparin
- trimethoprim

7.2 Lithium

Like other diuretics, ALDACTONE reduces the renal clearance of lithium, thus increasing the risk of lithium toxicity. Monitor lithium levels periodically when ALDACTONE is coadministered [see Clinical Pharmacology (12.3)].

7.3 Nonsteroidal Anti-Inflammatory Drugs (NSAIDs)

In some patients, the administration of an NSAID can reduce the diuretic, natriuretic, and antihypertensive effect of diuretics. Therefore, when ALDACTONE and NSAIDs are used concomitantly, monitor closely to determine if the desired effect of the diuretic is obtained [see Clinical Pharmacology (12.3)].

7.4 Digoxin

Spironolactone and its metabolites interfere with radioimmunoassays for digoxin and increase the apparent exposure to digoxin. It is unknown to what extent, if any, spironolactone may increase actual digoxin exposure. In patients taking concomitant digoxin, use an assay that does not interact with spironolactone.

7.5 Cholestyramine

Hyperkalemic metabolic acidosis has been reported in patients given ALDACTONE concurrently with cholestyramine.

7.6 Acetylsalicylic Acid

Acetylsalicylic acid may reduce the efficacy of spironolactone. Therefore, when ALDACTONE and acetylsalicylic acid are used concomitantly, ALDACTONE may need to be titrated to higher maintenance dose and the patient should be observed closely to determine if the desired effect is obtained [see Clinical Pharmacology (12.3)].

7.7 Abiraterone

Spironolactone binds to the androgen receptor and may increase prostate-specific antigen (PSA) levels in abiraterone-treated prostate cancer patients. Concomitant use of spironolactone and abiraterone is not recommended.

7.8 Mitotane

Avoid concomitant use of ALDACTONE and mitotane. Spironolactone reduces mitotane plasma levels [see Clinical Pharmacology (12.3)].

8 USE IN SPECIFIC POPULATIONS

8.1 Pregnancy

Risk Summary

Based on mechanism of action and findings in animal studies, spironolactone may affect sex differentiation of the male during embryogenesis (see Data). Rat embryofetal studies report feminization of male fetuses and endocrine dysfunction in females exposed to spironolactone in utero. Limited available data from published case reports and case series did not demonstrate an association of major malformations or other adverse pregnancy outcomes with spironolactone. There are risks to the mother and fetus associated with heart failure, cirrhosis and poorly controlled hypertension during pregnancy (see Clinical Considerations). Because of the potential risk to the male fetus due to anti-androgenic properties of spironolactone and animal data, avoid spironolactone in pregnant women or advise a pregnant woman of the potential risk to a male fetus.

The estimated background risk of major birth defects and miscarriage for the indicated population is unknown. All pregnancies have a background risk of birth defect, loss or other adverse outcomes. In the U.S. general population, the estimated background risk of major birth defects and miscarriage in clinically recognized pregnancies is 2%–4% and 15%–20%, respectively.

Clinical Considerations

Disease-Associated Maternal and/or Embryo/Fetal Risk

Pregnant women with congestive heart failure are at increased risk for preterm birth. Stroke volume and heart rate increase during pregnancy, increasing cardiac output, especially during the first trimester. Clinical classification of heart disease may worsen with pregnancy and lead to maternal death. Closely monitor pregnant patients for destabilization of their heart failure.

Pregnant women with symptomatic cirrhosis generally have poor outcomes including hepatic failure, variceal hemorrhage, preterm delivery, fetal growth restriction and maternal death. Outcomes are worse with coexisting esophageal varices. Pregnant women with cirrhosis of the liver should be carefully monitored and managed accordingly.

Hypertension in pregnancy increases the maternal risk for pre-eclampsia, gestational diabetes, premature delivery, and delivery complications (e.g., need for cesarean section, and post-partum hemorrhage). Hypertension increases the fetal risk for intrauterine growth restriction and intrauterine death.

Data

Animal Data

Teratology studies with ALDACTONE have been carried out in mice and rabbits at doses of up to 20 mg/kg/day. On a body surface area basis, this dose in the mouse is substantially below the maximum recommended human dose and, in the rabbit, approximates the maximum recommended human dose. No teratogenic or other embryotoxic effects were observed in mice, but the 20 mg/kg dose caused an increased rate of resorption and a lower number of live fetuses in rabbits. Because of its antiandrogenic activity and the requirement of testosterone for male morphogenesis, ALDACTONE may have the potential for adversely affecting sex differentiation of the male during embryogenesis. When administered to rats at 200 mg/kg/day between gestation days 13 and 21 (late embryogenesis and fetal development), feminization of male fetuses was observed. Offspring exposed during late pregnancy to 50 and 100 mg/kg/day doses of ALDACTONE exhibited changes in the reproductive tract including dose-dependent decreases in weights of the ventral prostate and seminal vesicle in males, ovaries and uteri that were enlarged in females, and other indications of endocrine dysfunction, that persisted into adulthood. ALDACTONE has known endocrine effects in animals including progestational and antiandrogenic effects.

8.2 Lactation

Risk Summary

Spironolactone is not present in breastmilk; however, limited data from a lactating woman at 17 days postpartum reports the presence of the active metabolite, canrenone, in human breast milk in low amounts that are expected to be clinically inconsequential. In this case, there were no adverse effects reported for the breastfed infant after short term exposure to spironolactone; however, long term effects on a breastfed infant are unknown. There are no data on spironolactone effects on milk production. Consider the developmental and health benefits of breastfeeding along with the mother's clinical need for spironolactone and any potential adverse effects on the breastfed child from spironolactone or from the underlying maternal condition.

8.4 Pediatric Use

Safety and effectiveness in pediatric patients have not been established.

8.5 Geriatric Use

ALDACTONE is substantially excreted by the kidney, and the risk of adverse reactions to this drug may be greater in patients with impaired renal function. Because elderly patients are more likely to have decreased renal function, monitor renal function.

8.6 Use in Renal Impairment

ALDACTONE is substantially excreted by the kidney, and the risk of adverse reactions to this drug may be greater in patients with impaired renal function. Patients with renal impairment are at increased risk of hyperkalemia. Monitor potassium closely.

8.7 Use in Hepatic Impairment

ALDACTONE can cause sudden alterations of fluid and electrolyte balance which may precipitate impaired neurological function, worsening hepatic encephalopathy and coma in patients with hepatic disease with cirrhosis and ascites. In these patients, initiate ALDACTONE in the hospital [see Dosage and Administration (2.4) and Clinical Pharmacology (12.3)].

Clearance of spironolactone and its metabolites is reduced in patients with cirrhosis. In patients with cirrhosis, start with lowest initial dose and titrate slowly [see Dosage and Administration (2.4) and Clinical Pharmacology (12.3)].

10 OVERDOSAGE

The oral LD50 of ALDACTONE is greater than 1000 mg/kg in mice, rats, and rabbits.

Acute overdosage of ALDACTONE may be manifested by drowsiness, mental confusion, maculopapular or erythematous rash, nausea, vomiting, dizziness, or diarrhea. Rarely, instances of hyponatremia, hyperkalemia, or hepatic coma may occur in patients with severe liver disease, but these are unlikely due to acute overdosage. Hyperkalemia may occur, especially in patients with impaired renal function.

Treatment: Induce vomiting or evacuate the stomach by lavage. There is no specific antidote. Treatment is supportive to maintain hydration, electrolyte balance, and vital functions. Patients who have renal impairment may develop hyperkalemia. In such cases, discontinue ALDACTONE.

11 DESCRIPTION

ALDACTONE oral tablets contain 25 mg, 50 mg, or 100 mg of the aldosterone antagonist spironolactone, 17-hydroxy-7α-mercapto-3-oxo-17α-pregn-4-ene-21-carboxylic acid γ-lactone acetate, which has the following structural formula:

Spironolactone is practically insoluble in water, soluble in alcohol, and freely soluble in benzene and in chloroform.

Inactive ingredients include calcium sulfate, corn starch, flavor, hypromellose, iron oxide, magnesium stearate, polyethylene glycol, povidone, and titanium dioxide.

12 CLINICAL PHARMACOLOGY

12.1 Mechanism of Action

Spironolactone and its active metabolites are specific pharmacologic antagonists of aldosterone, acting primarily through competitive binding of receptors at the aldosterone-dependent sodium-potassium exchange site in the distal convoluted renal tubule. Spironolactone causes increased amounts of sodium and water to be excreted, while potassium is retained. Spironolactone acts both as a diuretic and as an antihypertensive drug by this mechanism. It may be given alone or with other diuretic agents that act more proximally in the renal tubule.

12.2 Pharmacodynamics

Aldosterone antagonist activity: Increased levels of the mineralocorticoid, aldosterone, are present in primary and secondary hyperaldosteronism. Edematous states in which secondary aldosteronism is usually involved include congestive heart failure, hepatic cirrhosis, and nephrotic syndrome. By competing with aldosterone for receptor sites, spironolactone provides effective therapy for the edema and ascites in those conditions. Spironolactone counteracts secondary aldosteronism induced by the volume depletion and associated sodium loss caused by active diuretic therapy.

12.3 Pharmacokinetics

Absorption

The mean time to reach peak plasma concentration of spironolactone and the active metabolite, canrenone, in healthy volunteers is 2.6 and 4.3 hours, respectively.

Effect of food: Food increased the bioavailability of spironolactone (as measured by AUC) by approximately 95.4%. Patients should establish a routine pattern for taking ALDACTONE with regard to meals [see Dosage and Administration (2.1)].

Distribution

Spironolactone and its metabolites are more than 90% bound to plasma proteins.

Elimination

The mean half-life of spironolactone is 1.4 hour. The mean half-life values of its metabolites including canrenone, 7-α-(thiomethyl) spirolactone (TMS), and 6-β-hydroxy-7-α-(thiomethyl) spirolactone (HTMS) are 16.5, 13.8, and 15 hours, respectively.

Metabolism: Spironolactone is rapidly and extensively metabolized. Metabolites can be divided into two main categories: those in which sulfur of the parent molecule is removed (e.g., canrenone) and those in which the sulfur is retained (e.g., TMS and HTMS). In humans, the potencies of TMS and 7-α-thiospirolactone in reversing the effects of the synthetic mineralocorticoid, fludrocortisone, on urinary electrolyte composition were approximately a third relative to spironolactone. However, since the serum concentrations of these steroids were not determined, their incomplete absorption and/or first-pass metabolism could not be ruled out as a reason for their reduced in vivo activities.

Excretion: The metabolites are excreted primarily in the urine and secondarily in bile.

Specific Populations

The impact of age, sex, race/ethnicity, and renal impairment on the pharmacokinetics of spironolactone have not been specifically studied.

Patients with Hepatic Impairment: The terminal half-life of spironolactone has been reported to be increased in patients with cirrhotic ascites [see Use in Specific Populations (8.7)].

Drug Interaction Studies:

Drugs and Supplements Increasing Serum Potassium: Concomitant administration of ALDACTONE with potassium supplementation, salt substitutes containing potassium, a diet rich in potassium, or drugs that can increase potassium, including ACE inhibitors, angiotensin II antagonists, non-steroidal anti-inflammatory drugs (NSAIDs), heparin and low molecular weight heparin, may lead to severe hyperkalemia [see Warnings and Precautions (5.1)and Drug Interactions (7.1)].

Lithium: ALDACTONE reduces the renal clearance of lithium, inducing a high risk of lithium toxicity [see Drug Interactions (7.2)].

Nonsteroidal Anti-Inflammatory Drugs (NSAIDs): In some patients, the administration of an NSAID can reduce the diuretic, natriuretic, and antihypertensive effect of loop, potassium-sparing, and thiazide diuretics [see Drug Interactions (7.3)].

Acetylsalicylic acid: A single dose of 600 mg of acetylsalicylic acid inhibited the natriuretic effect of spironolactone, which was hypothesized be due to inhibition of tubular secretion of canrenone, causing decreased effectiveness of spironolactone [see Drug Interactions (7.6)].

Mitotane: The effect of concomitant spironolactone on the pharmacokinetics of mitotane has not been studied; however, patients exhibited significantly lower mitotane levels compared to those who did not receive concomitant spironolactone despite receiving higher mitotane doses [see Drug Interactions (7.8)].

13 NONCLINICAL TOXICOLOGY

13.1 Carcinogenesis, Mutagenesis, Impairment of Fertility

Carcinogenesis

Orally administered ALDACTONE has been shown to be a tumorigen in dietary administration studies performed in Sprague Dawley rats, with its proliferative effects manifested on endocrine organs and the liver. In an 18-month study using doses of about 50, 150, and 500 mg/kg/day, there were statistically significant increases in benign adenomas of the thyroid and testes and, in male rats, a dose-related increase in proliferative changes in the liver (including hepatocytomegaly and hyperplastic nodules). In 24-month studies in which rats were administered doses of about 10, 30, 100, and 150 mg ALDACTONE/kg/day, the range of proliferative effects included significant increases in hepatocellular adenomas and testicular interstitial cell tumors in males, and significant increases in thyroid follicular cell adenomas and carcinomas in both sexes. There was also a statistically significant increase in benign uterine endometrial stromal polyps in females.

Mutagenesis

Neither ALDACTONE nor potassium canrenoate produced mutagenic effects in tests using bacteria or yeast. In the absence of metabolic activation, neither ALDACTONE nor potassium canrenoate has been shown to be mutagenic in mammalian tests in vitro. In the presence of metabolic activation, ALDACTONE has been reported to be negative in some mammalian mutagenicity tests in vitro and inconclusive (but slightly positive) for mutagenicity in other mammalian tests in vitro. In the presence of metabolic activation, potassium canrenoate has been reported to test positive for mutagenicity in some mammalian tests in vitro, inconclusive in others, and negative in still others.

Impairment of Fertility

In a three-litter reproduction study in which female rats received dietary doses of 15 and 50 mg ALDACTONE/kg/day, there were no effects on mating and fertility, but there was a small increase in incidence of stillborn pups at 50 mg/kg/day. When injected into female rats (100 mg/kg/day for 7 days, i.p.), ALDACTONE was found to increase the length of the estrous cycle by prolonging diestrus during treatment and inducing constant diestrus during a two-week post-treatment observation period. These effects were associated with retarded ovarian follicle development and a reduction in circulating estrogen levels, which would be expected to impair mating, fertility, and fecundity. ALDACTONE (100 mg/kg/day), administered i.p. to female mice during a two-week cohabitation period with untreated males, decreased the number of mated mice that conceived (effect shown to be caused by an inhibition of ovulation) and decreased the number of implanted embryos in those that became pregnant (effect shown to be caused by an inhibition of implantation), and at 200 mg/kg, also increased the latency period to mating.

14 CLINICAL STUDIES

14.1 Heart Failure

The Randomized Aldactone Evaluation Study (RALES) was a placebo controlled, double-blind study of the effect of spironolactone on mortality in patients with highly symptomatic heart failure and reduced ejection fraction. To be eligible to participate patients had to have an ejection fraction of ≤ 35%, NYHA class III–IV symptoms, and a history of NYHA class IV symptoms within the last 6 months before enrollment. Patients with a baseline serum creatinine of >2.5 mg/dL or a recent increase of 25% or with a baseline serum potassium of >5.0 mEq/L were excluded.

Follow-up visits and laboratory measurements (including serum potassium and creatinine) were performed every four weeks for the first 12 weeks, then every 3 months for the first year, and then every 6 months thereafter.

The initial dose of spironolactone was 25 mg once daily. Patients who were intolerant of the initial dosage regimen had their dose decreased to one 25 mg tablet every other day at one to four weeks. Patients who were tolerant of one tablet daily at 8 weeks may have had their dose increased to 50 mg daily at the discretion of the investigator. The mean daily dose at study end for patients randomized to spironolactone was 26 mg.

1663 patients were randomized 1:1 to spironolactone or placebo. 87% of patients were white, 7% black, 2% Asian. 73% were male and median age was 67. The median ejection fraction was 26%. 70% were NYHA class III and 29% class IV. The etiology of heart failure was ischemic in 55%, and non-ischemic in 45%. There was a history of myocardial infarction in 28%, of hypertension in 24%, and of diabetes in 22%. The median baseline serum creatinine was 1.2 mg/dL and the median baseline creatinine clearance was 57 mL/min.

At baseline 100% of patients were taking loop diuretic and 95% were taking an ACE inhibitor. Other medications used at any time during the study included digoxin (78%), anticoagulants (58%), aspirin (43%), and beta-blockers (15%).

The primary endpoint for RALES was time to all-cause mortality. RALES was terminated early because of significant mortality benefit demonstrated during a planned interim analysis. Compared to placebo, spironolactone reduced the risk of death by 30% (p<0.001; 95% confidence interval 18% to 40%). Spironolactone also reduced the risk of hospitalization for cardiac causes (defined as worsening heart failure, angina, ventricular arrhythmias, or myocardial infarction) by 30% (p <0.001; 95% confidence interval 18% to 41%).

The survival curves by treatment group are shown in Figure 1.

Figure 1. Survival by Treatment Group in RALES

Mortality hazard ratios for some subgroups are shown in Figure 2. The favorable effect of spironolactone on mortality appeared similar for both genders and all age groups except patients younger than 55. There were too few non-whites in RALES to evaluate if the effects differ by race. Spironolactone's benefit appeared greater in patients with low baseline serum potassium levels and less in patients with ejection fractions <0.2. These subgroup analyses must be interpreted cautiously.

Figure 2. Hazard Ratios of All-Cause Mortality by Subgroup in RALES

Figure 2: The size of each box is proportional to the sample size as well as the event rate. LVEF denotes left ventricular ejection fraction, Ser Creatinine denotes serum creatinine, Cr Clearance denotes creatinine clearance, and ACEI denotes angiotensin-converting enzyme inhibitor.

14.2 Hypertension

The dose response of spironolactone for hypertension has not been well characterized. In patients with hypertension, decreases in systolic blood pressure have been observed at doses ranging from 25 to 100 mg/day. Doses greater than 100 mg/day generally do not provide additional reductions in blood pressure [see Dosage and Administration (2.3)].

16 HOW SUPPLIED/STORAGE AND HANDLING

ALDACTONE 25 mg tablets are round, light yellow, film-coated, with SEARLE and 1001 debossed on one side and ALDACTONE and 25 on the other side, supplied as:

NDC Number | Size
0025-1001-31 | bottle of 100

ALDACTONE 50 mg tablets are oval, light orange, scored, film-coated, with SEARLE and 1041 debossed on the scored side and ALDACTONE and 50 on the other side, supplied as:

NDC Number | Size
0025-1041-31 | bottle of 100

ALDACTONE 100 mg tablets are round, peach-colored, scored, film-coated, with SEARLE and 1031 debossed on the scored side and ALDACTONE and 100 on the other side, supplied as:

NDC Number | Size
0025-1031-31 | bottle of 100

STORAGE AND HANDLING

Store below 77°F (25°C).

17 PATIENT COUNSELING INFORMATION

Patients who receive ALDACTONE should be advised to avoid potassium supplements and foods containing high levels of potassium, including salt substitutes.

This product's label may have been updated. For current full prescribing information, please visit www.pfizer.com.

LAB-0231-18.0

PRINCIPAL DISPLAY PANEL - 25 mg Tablet Bottle Label

Pfizer

NDC 0025-1001-31

Aldactone®
(spironolactone)
tablets, USP

25 mg

100 Tablets
Rx only

PRINCIPAL DISPLAY PANEL - 50 mg Tablet Bottle Label

Pfizer

NDC 0025-1041-31

Aldactone®
(spironolactone)
tablets, USP

50 mg

100 Tablets
Rx only

PRINCIPAL DISPLAY PANEL - 100 mg Tablet Bottle Label

Pfizer

NDC 0025-1031-31

Aldactone®
(spironolactone)
tablets, USP

100 mg

100 Tablets
Rx only